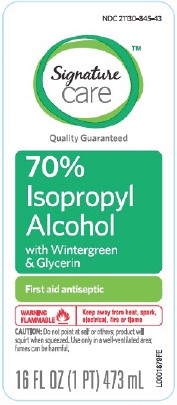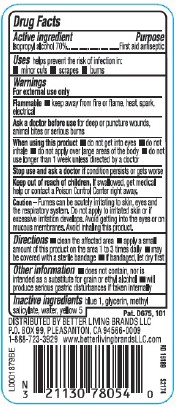 DRUG LABEL: Isopropyl Alcohol
NDC: 21130-845 | Form: LIQUID
Manufacturer: Better Living Brands, LLC
Category: otc | Type: HUMAN OTC DRUG LABEL
Date: 20260224

ACTIVE INGREDIENTS: ISOPROPYL ALCOHOL 70 mL/100 mL
INACTIVE INGREDIENTS: FD&C YELLOW NO. 5; FD&C BLUE NO. 1; GLYCERIN; METHYL SALICYLATE; WATER

Signature Care 845.003/845AE
70% IPA, Wintergreen

Active ingredient

Isopropyl alcohol 70%

Purpose

First aid antiseptic

Uses

helps prevent the risk of infection in:

- minor cuts
- scrapes
- burns

Warnings

For external use only

Flammable. Keep away from fire or flame, heat, spark, electrical.

Ask a doctor before use

for deep or puncture wounds, animal bites or serious burns

When using this product

- do not get into eyes
- do not inhale
- do not apply over large areas of the body
- do not use longer than 1 week unless directed by a doctor

Stop use and ask a doctor if

condition persists or gets worse

Keep out of reach of children.

If swallowed, get medical help or contact a Poison Control Center right away.

Caution

Fumes can be acutely irritating to skin, eyes and the respiratory system. Do not apply to irritated skin or if excessive irritation develops. Avoid gettting into the eyes or on mucous membranes. Avoid inhaling this product.

Directions

- clean the affected area
- apply a small amount of this product on the area 1 to 3 times daily
- may be covered with a sterile bandage
- if bandaged, let dry first

Other information

- does not contain, nor is intended as a substitute for grain or ethyl alcohol
- will product serious gastric disturbances if taken internally

Inactive ingredients

blue 1, glycerin, methyl salicylate, water, yellow 5

ADVERSE REACTION

DISTRIBUTED BY LIVING BRANDS LLC

P.O. BOX 99, PLEASANTON, CAN 94566-0009

1-888-723-3929 www.betterlivingbrandsLLC.com

Pat. D675, 101

principal display panel

NDC 2130-845-43

Signature Care™

Quality Guaranteed

70% Isopropyl Alcohol with Wintergreen & Glycerin

First Aid Antiseptic

WARNING FLAMMABLE - Keep away from heat, spark, electrical, fire or flame

CAUTION: Do not point at self or others; product will squirt when squeezed. Use only in a well-ventilated area. Fumes can be harmful.

16 FL OZ (1 PT) 473 mL